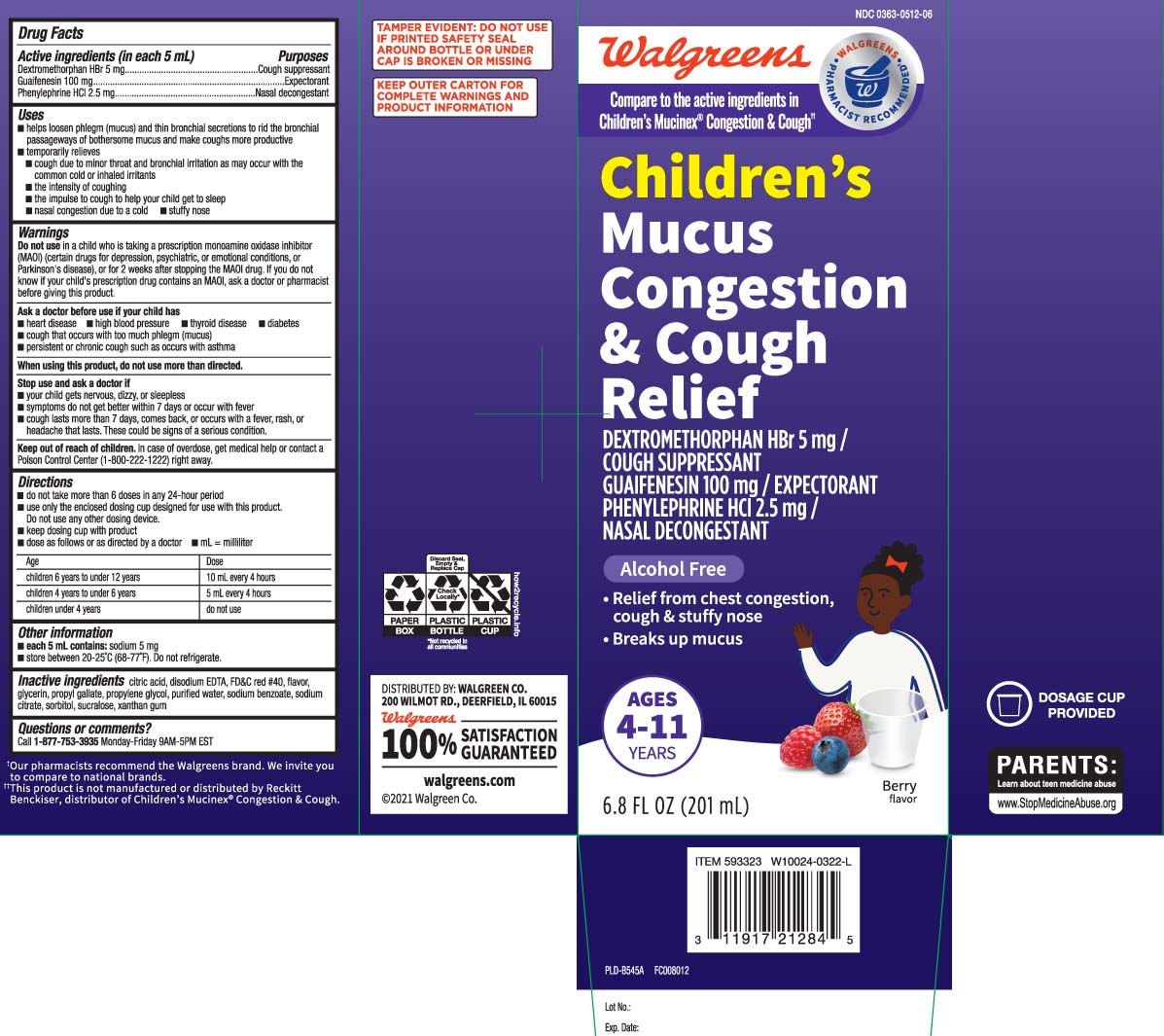 DRUG LABEL: Mucus Congestion and Cough Relief
NDC: 0363-0512 | Form: LIQUID
Manufacturer: Walgreens
Category: otc | Type: HUMAN OTC DRUG LABEL
Date: 20240508

ACTIVE INGREDIENTS: DEXTROMETHORPHAN HYDROBROMIDE 5 mg/5 mL; GUAIFENESIN 100 mg/5 mL; PHENYLEPHRINE HYDROCHLORIDE 2.5 mg/5 mL
INACTIVE INGREDIENTS: ANHYDROUS CITRIC ACID; FD&C RED NO. 40; GLYCERIN; PROPYLENE GLYCOL; WATER; SUCRALOSE; XANTHAN GUM; EDETATE DISODIUM; PROPYL GALLATE; SODIUM BENZOATE; SODIUM CITRATE; SORBITOL

Drug Facts

Active ingredients (in each 5 mL)

Dextromethorphan HBr 5 mg

Guaifenesin 100 mg

Phenylephrine HCI 2.5 mg

Purposes

Cough suppressant

Expectorant

Nasal decongestant

Uses

- helps loosen phlegm (mucus) and thin bronchial secretions to rid the bronchial passageways of bothersome mucus and make coughs more productive
- temporarily relieves:
  - cough due to minor throat and bronchial irritation as may occur with the common cold or inhaled irritants
  - the intensity of coughing
  - the impulse to cough to help your child get to sleep
  - nasal congestion due to a cold
  - stuffy nose

Warnings

Do not use

- in a child who is taking a prescription monoamine oxidase inhibitor (MAOI) (certain drugs for depression, psychiatric or emotional conditions, or Parkinson's disease), or for 2 weeks after stopping the MAOI drug. If you do not know if your child's prescription drug contains an MAOI, ask a doctor or pharmacist before taking this product.

Ask a doctor before use if the child has

- heart disease
- high blood pressure
- thyroid disease
- diabetes
- cough that occurs with too much phlegm (mucus)
- persistent or chronic cough such as occurs with asthma

When using this product,

do not use more than directed.

Stop use and ask a doctor if

- your child gets nervous, dizzy, or sleepless
- symptoms do not get better within 7 days or occur with fever
- cough lasts more than 7 days, comes back, or occurs with fever, rash, or headache that lasts. These could be signs of a serious condition.

Keep out of reach of children.

In case of overdose, get medical help or contact a Poison Control Center (1-800-222-1222) right away.

Directions

- do not take more than 6 doses in any 24-hour period
- use only the enclosed dosing cup designed for use with this product. Do not use any other dosing device.
- keep dosing cup with product
- dose as follows or as directed by a doctor
- mL = milliliter

age | dose
children 6 years to under 12 years | 10 mL every 4 hours
children 4 years to under 6 years | 5 mL every 4 hours
children under 4 years | do not use

Other information

- each 5 mL contains: sodium 5 mg
- store between 20-25ºC (68-77ºF). Do not refrigerate.

Inactive ingredients

anhydrous citric acid, disodium EDTA, FD&C red #40, flavor, glycerin, propyl gallate, propylene glycol, purified water, sodium benzoate, sodium citrate, sorbitol, sucralose, xanthan gum

Questions or comments?

Call 1-877-753-3935 Monday-Friday 9AM-5PM EST

Principal Display Panel

Compare to the active ingredients in Children's Mucinex® Congestion & Cough††

Children's

Mucus Congestion & Cough Relief

DEXTROMETHORPHAN HBr 5 mg /

COUGH SUPPRESSANT

GUAIFENESIN 100 mg /

EXPECTORANT

PHENYLEPHRINE HCI 2.5 mg /

NASAL DECONGESTANT

Alcohol Free

- Relief from chest congestion, cough & stuffy nose
- Breaks up mucus

AGES 4 - 11 YEARS

Berry flavor

DOSAGE CUP PROVIDED

FL OZ (mL)

††This product is not manufactured or distributed by Reckitt Benckiser, distributor of Children's Mucinex® Congestion & Cough.

TAMPER EVIDENT: DO NOT USE IF PRINTED SAFETY SEAL AROUND BOTTLE OR UNDER CAP IS BROKEN OR MISSING.

KEEP OUTER CARTON FOR COMPLETE WARNINGS AND PRODUCT INFORMATION.

DISTRIBUTED BY: WALGREEN CO.

200 WILMOT RD., DEERFIELD, IL 60015

walgreens.com

Package Label

WALGREENS Children's Mucus Congestion & Cough Berry Flavor